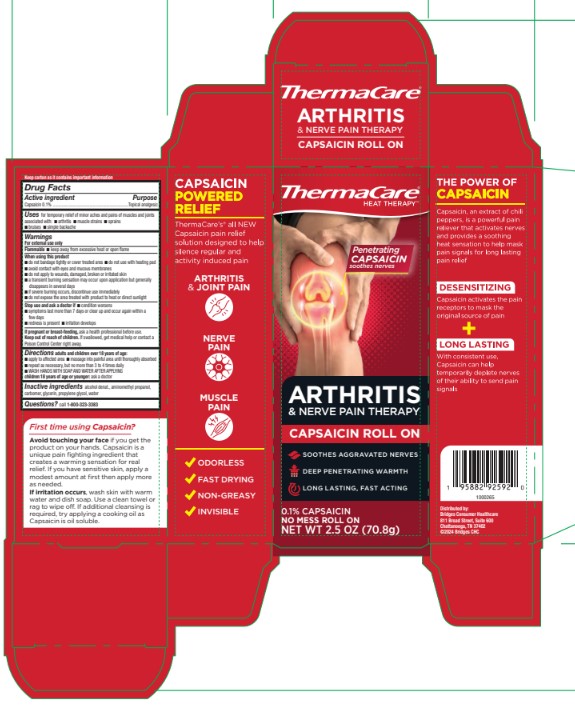 DRUG LABEL: Thermacare Arthritis and Nerve Pain Therapy Capsaicin Roll On
NDC: 69693-001 | Form: LIQUID
Manufacturer: Clarion Brands LLC
Category: otc | Type: HUMAN OTC DRUG LABEL
Date: 20241202

ACTIVE INGREDIENTS: CAPSAICIN 0.1 g/100 g
INACTIVE INGREDIENTS: ALCOHOL; CARBOMER INTERPOLYMER TYPE A (ALLYL SUCROSE CROSSLINKED); WATER; GLYCERIN; AMINOMETHYL PROPANOL; PROPYLENE GLYCOL

ACTIVE INGREDIENT

Capsaicin 0.1%

PURPOSE

Topical analgesic

INDICATIONS AND USAGE

For temporary relief of minor aches and pains of muscles and joints associated with:

- arthritis
- muscle strains
- sprains
- bruises
- simple backache

WARNINGS

For external use only

Flammable

- keep away from excessive heat or open flame

Stop use and ask a doctor if

- condition worsens
- symptoms last more than 7 days or clear up and occur again within a few days
- redness is present
- irritation develops

If pregnant or breast-feeding,

ask a health professional before use.

When using this product

- do not bandage tightly or cover treated area
- do not use with heating pad
- avoid contact with eyes and mucous membranes
- do not apply to wounds, damaged, broken or irritated skin
- a transient burning sensation may occur upon application but generally disappears in several days
- if severe burning occurs, discontinue use immediately
- do not expose the area treated with product to heat or direct sunlight

Directions adults and children over 18 years of age:

- apply to affected area
- massage into painful area until thoroughly absorbed
- repeat as necessary, but no more than 3 to 4 times daily
- wash hands with soap and water after applying

INACTIVE INGREDIENT

alcohol denatured

aminomethyl propanol

carbomer

glycerin

propylene glycol

water

QUESTIONS

call 1-800-323-3383

DOSAGE AND ADMINISTRATION

Capsaicin 0.1%

Topical analgesic

Keep out of reach of children. If swallowed, get medical help or contact a Poison Control Center right away.

Children 18 years of age or younger: ask a doctor

PACKAGE LABEL

Thermacare Heat Therapy™

Penetraing CAPSAICIN soothes nerves

ARTHRITIS & NERVE PAIN THERAPY

CAPSAICIN ROLL ON

Soothes Aggravated Nerves

Deep Penetrating Warmth

Long Lasting, Fast Acting

0.1% Capsaicin

No Mess Roll On

NET WT. 2.5 oz (70.8 g)